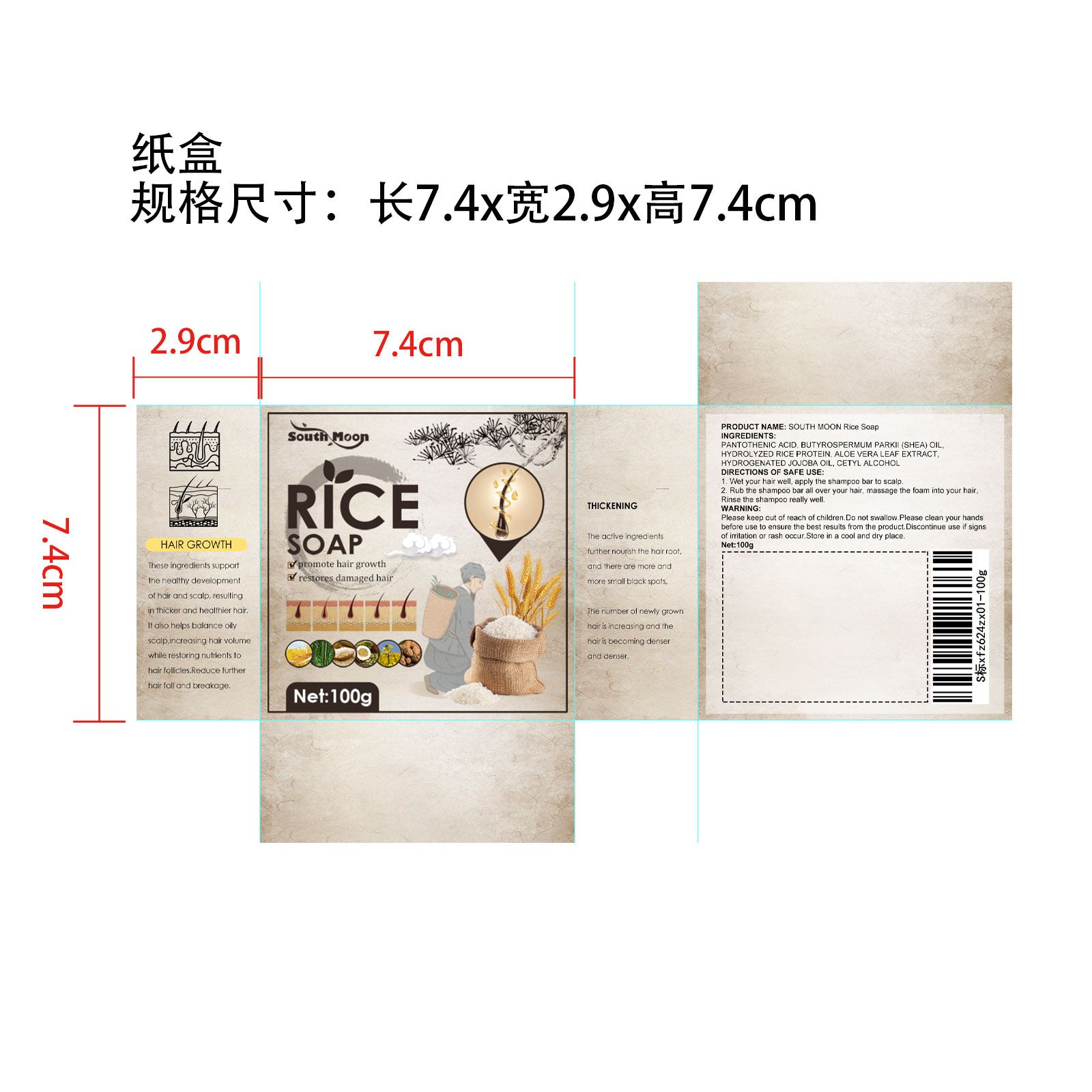 DRUG LABEL: RiceShampooSoap
NDC: 84778-018 | Form: SOAP
Manufacturer: Guangzhou Yixin Cross-border E-commerce Co., Ltd.
Category: otc | Type: HUMAN OTC DRUG LABEL
Date: 20241029

ACTIVE INGREDIENTS: HYDROLYZED RICE PROTEIN (ENZYMATIC; 2000 MW) 6 g/6 g
INACTIVE INGREDIENTS: FRAGRANCE 13576; BEHENTRIMONIUM METHOSULFATE; STEARIC ACID; ALOE VERA LEAF; SODIUM COCOYL ISETHIONATE; CETYL ALCOHOL; SODIUM LACTATE

COMPONENTS

Hydrolyzed Rice Protein 6g

PURPOSE

Deep cleans the hair and scalp, strengthens and moisturizes the hair, makes the hair soft and shiny, and promotes hair health

INDICATIONS AND USAGE

Strengthens hair roots and promotes healthy hair growth

WARNINGS

For external use only

DOSAGE AND ADMINISTRATION

For external use only

When using this product, avoid contact with eyes. If contact with eyes occurs, rinse immediately with clean water. If allergic or irritating reaction occurs, stop use and consult a doctor. Keep this product out of reach of children. For external use only, not to be swallowed.

WHEN USING

If allergic or irritation occurs, discontinue use and consult a doctor

Keep out of reach of children.lf swallowed, get medical help or contacta Poison Control Center right away.

INACTIVE INGREDIENT

Sodium Cocoyl Isethionate
Behentrimonium Methosulfate
Cocoa Butter Glyceryl Esters

Cetyl Alcohol
Shea Butter Oleyl Esters

Stearic Acid

Rice Bran Oil Polyglyceryl-3 Esters
Broccoli Seed Oil Polyglyceryl-4 Esters
Sodium Lactate
Aloe Vera Leaf Extract
Jojoba Oil PEG-8 Esters
Fragrance